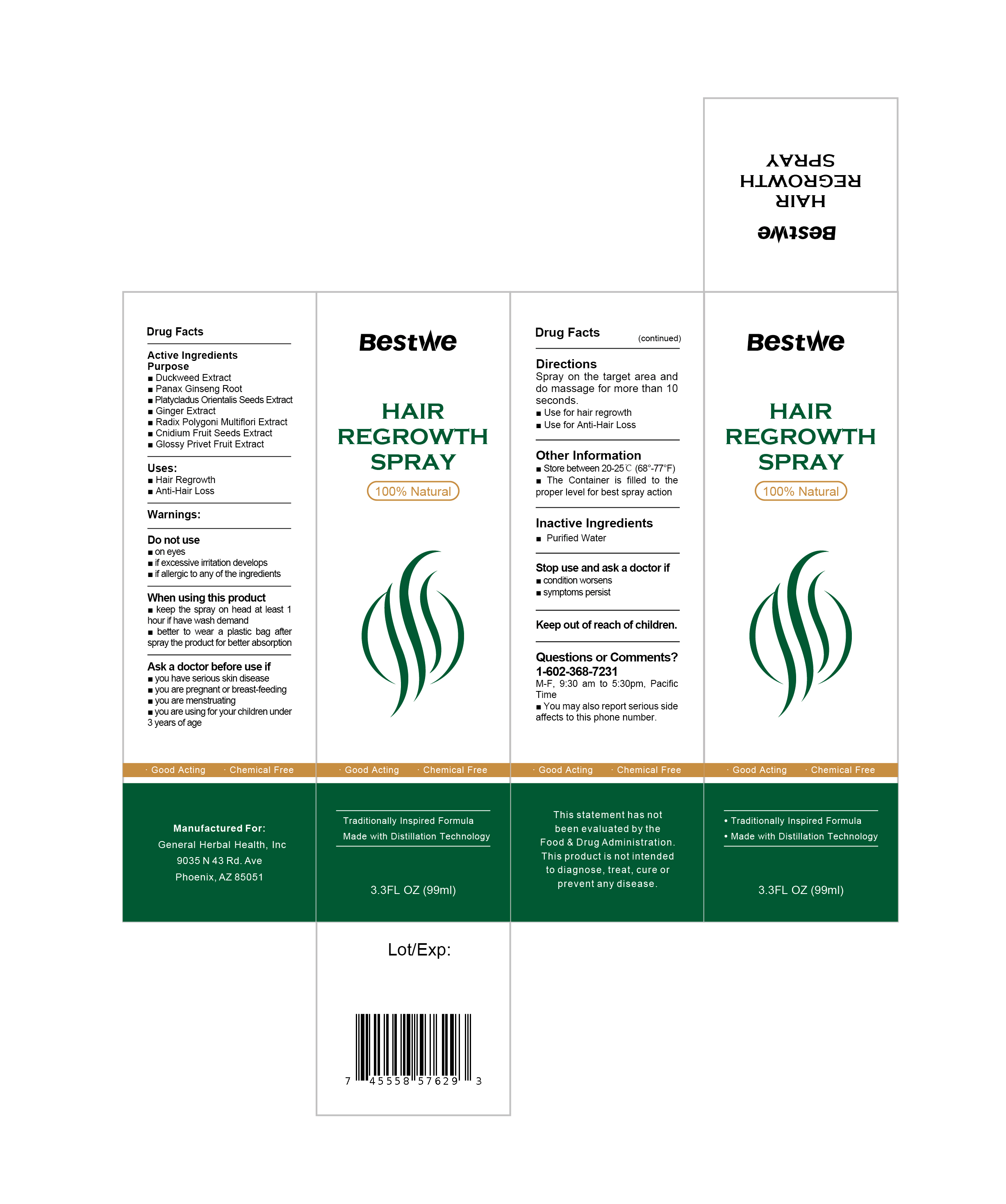 DRUG LABEL: Bestwe Hair Growth Tonic
NDC: 87325-001 | Form: LIQUID
Manufacturer: Yantai Dupont Daily Necessities Co., Ltd.
Category: otc | Type: HUMAN OTC DRUG LABEL
Date: 20260111

ACTIVE INGREDIENTS: ZINGIBER OFFICINALE (GINGER) ROOT OIL 0.5 g/100 g; POLYGONUM CUSPIDATUM ROOT 0.12 g/100 g; PANAX GINSENG ROOT 0.35 g/100 g; LIGUSTRUM LUCIDUM FRUIT 0.5 g/100 g; CNIDIUM MONNIERI FRUIT 0.001 g/100 g; LEMNA MINOR 2.739 g/100 g; PLATYCLADUS ORIENTALIS SEED 0.5 g/100 g
INACTIVE INGREDIENTS: WATER

Active Ingredients

■ Duckweed Extract
■ Panax Ginseng Root
■ Platycladus Orientalis Seeds Extract
■ Ginger Extract
■ Radix Polygoni Multiflori Extract
■ Cnidium Fruit Seeds Extract
■ Glossy Privet Fruit Extract

Uses：

■ Hair Rgerowth
■ Anti-Hair Loss

Inactive Ingredients

■ Purified Water

INDICATIONS AND USAGE

Spray on the target area and do massage for more than 10 seconds.
■ Use for hair regrowth
■ Use for Anti-Hair Loss

Directions

Spray on the target area and do massage for more than 10 seconds.
■ Use for hair regrowth
■ Use for Anti-Hair Loss

When using this product

■ keep the spray on head at least 1 hour if have wash demand

■ better to wear a plastic bag after spray the product for better absorption

Ask a doctor before use if

■ you have serious skin disease
■ you are pregnant or reast-feeding
■ you are menstruating
■ you are using for your children under 3 years of age

Stop use and ask a doctor if

■ condition worsens
■ symptoms persist

Keep out of reach of children.

Warnings:

Do not use
■ on eyes
■ if excessive irritation develops
■ if allergic to any of the ingredients

Other information

■ Store between 20-25℃(68° to 77°F)
■ The Container is filled to the proper level for best spra action

Manufactured For:

Manufactured For:General Herbal Health,Inc 9035 N 43 Rd.Ave Phoenix,AZ 85051

Questions or Comments?

1-602-368-7231
M-F,9:30 am to 5:30pm,Pacific Time
■ You may also report serious side affects to this phone number.